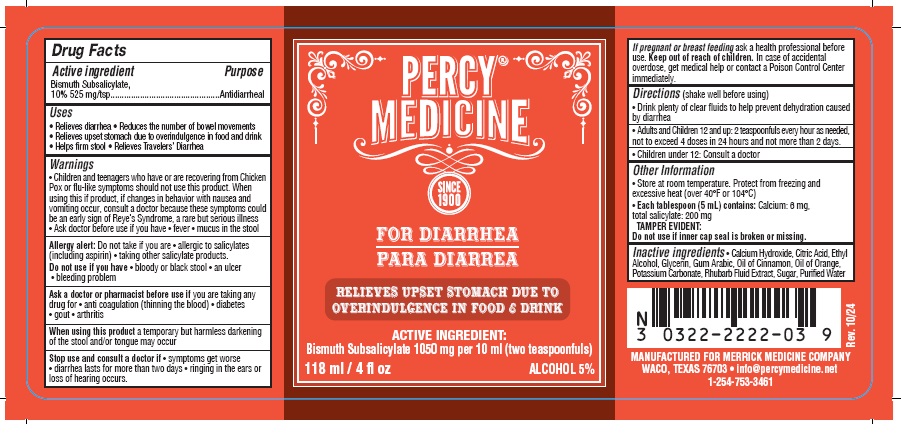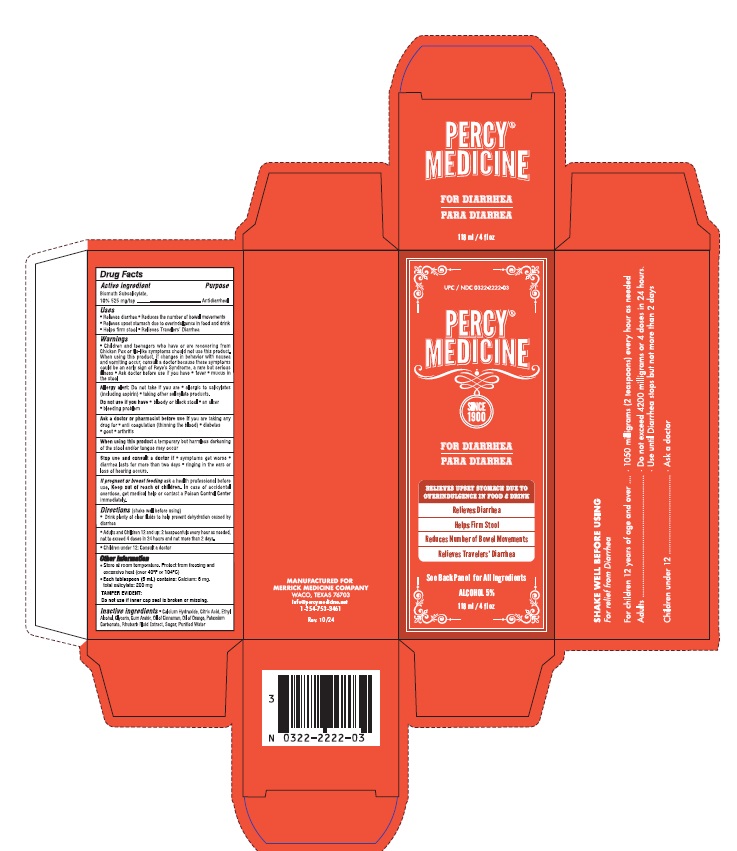 DRUG LABEL: Percy Medicine
NDC: 0322-2222 | Form: LIQUID
Manufacturer: Merrick Medicine Company, Inc
Category: otc | Type: HUMAN OTC DRUG LABEL
Date: 20251111

ACTIVE INGREDIENTS: BISMUTH SUBSALICYLATE 1050 mg/10 mL
INACTIVE INGREDIENTS: WATER; CALCIUM HYDROXIDE; CITRIC ACID MONOHYDRATE; ALCOHOL; GLYCERIN; ACACIA; ORANGE OIL; CINNAMON OIL; POTASSIUM CARBONATE; RHUBARB; SUCROSE

PERCY MEDICINE

Drug Facts Active Ingredient

Active Ingredients

Bismuth Subsalicylate

Purpose

Antidiarrheal

Warnings

Children and teenagers that have or are recovering from Chicken Pox, flu systems, or flue should NOT use this product. If nausea, vomiting, or fever occur, consult a doctor because these symptoms could be an early sign of Reye Syndrome, a rare but serious condition.

Allergy Alert: Contains Salicylates. Do Not take if you are - allergic to salicylates (including aspirin) - taking other salicylate products.

Do not use if you have - blood or black stool - an ulcer - bleeding problem.

Ask a doctor before use if you are taking any drug for anti coagulation (thinning of the blood), diabetes,gout, arthritis. - When using this product a temporary but harmless darkening of the stool and/or tongue may occur.

Stop use and consult a doctor if - symptoms get worse - ringing in the ears or loss of hearing occurs - diarrhea lasts more that 2 days.

if pregnant or breast feeding ask a professional before use. In case of accidental overdose, get medical help or contact a Poison Control Center immediately.

Inactive Ingredients

INACTIVE INGREDIENTS: CALCIUM HYDROXIDE, CITRIC ACID, ETHYL ALCOHOL, GLYCERINE, GUM ARABIC, OIL OF CINNAMON, OIL OF ORANGE, POTASSIUM CARBONATE, RHUBARB FLUID EXTRACT, SUGAR, PURIFIED WATER

Directions

(shake well before using)

Adults and children 12 yrs and over : 2 teaspoonfuls every hour as needed , not to exceed 4 doses in 24 hours and not more than 2 days.

Children under 12: Consult a doctor.

Keep out of reach of children

Uses:

Relieves diarrhea, reduces number of bowel movements.

Helps firm stool.

Relieves nausea, heartburn, fullness due to overindulgence of food and drink.

Package Label

=======================================================
PERCY MEDICINE
FOR DIARRHEA

MANUFACTURED FOR
MERRICK MEDICINE COMPANY
WACO, TEXAS 76703
info@percymedicine.net
1-254-753-3461

Carton Label

Bottle Label

res